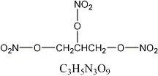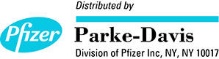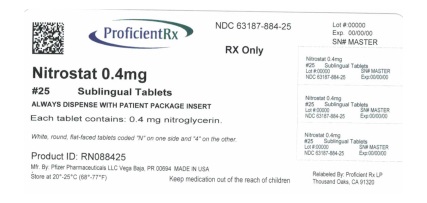 DRUG LABEL: Nitrostat
NDC: 63187-884 | Form: TABLET
Manufacturer: Proficient Rx LP
Category: prescription | Type: HUMAN PRESCRIPTION DRUG LABEL
Date: 20191101

ACTIVE INGREDIENTS: NITROGLYCERIN 0.4 mg/1 1
INACTIVE INGREDIENTS: LACTOSE MONOHYDRATE; GLYCERYL MONOSTEARATE; CALCIUM STEARATE; SILICON DIOXIDE; STARCH, CORN

Nitrostat®
(Nitroglycerin Sublingual Tablets, USP)

DESCRIPTION

NITROSTAT is a stabilized sublingual compressed nitroglycerin tablet that contains 0.3 mg, 0.4 mg , or 0.6 mg nitroglycerin; as well as lactose monohydrate, NF; glyceryl monostearate, NF; pregelatinized starch, NF; calcium stearate, NF powder; and silicon dioxide, colloidal, NF.

Nitroglycerin, an organic nitrate, is a vasodilating agent. The chemical name for nitroglycerin is 1, 2, 3 propanetriol trinitrate and the chemical structure is:

Molecular weight: 227.09

CLINICAL PHARMACOLOGY

The principal pharmacological action of nitroglycerin is relaxation of vascular smooth muscle. Although venous effects predominate, nitroglycerin produces, in a dose-related manner, dilation of both arterial and venous beds. Dilation of postcapillary vessels, including large veins, promotes peripheral pooling of blood, decreases venous return to the heart, and reduces left ventricular end-diastolic pressure (preload). Nitroglycerin also produces arteriolar relaxation, thereby reducing peripheral vascular resistance and arterial pressure (afterload), and dilates large epicardial coronary arteries; however, the extent to which this latter effect contributes to the relief of exertional angina is unclear.

Therapeutic doses of nitroglycerin may reduce systolic, diastolic, and mean arterial blood pressure. Effective coronary perfusion pressure is usually maintained, but can be compromised if blood pressure falls excessively, or increased heart rate decreases diastolic filling time.

Elevated central venous and pulmonary capillary wedge pressures, and pulmonary and systemic vascular resistance are also reduced by nitroglycerin therapy. Heart rate is usually slightly increased, presumably due to a compensatory response to the fall in blood pressure. Cardiac index may be increased, decreased, or unchanged. Myocardial oxygen consumption or demand (as measured by the pressure-rate product, tension-time index, and stroke-work index) is decreased and a more favorable supply-demand ratio can be achieved. Patients with elevated left ventricular filling pressures and increased systemic vascular resistance in association with a depressed cardiac index are likely to experience an improvement in cardiac index. In contrast, when filling pressures and cardiac index are normal, cardiac index may be slightly reduced following nitroglycerin administration.

Mechanism of Action

Nitroglycerin forms free radical nitric oxide (NO) which activates guanylate cyclase, resulting in an increase of guanosine 3'5' monophosphate (cyclic GMP) in smooth muscle and other tissues. These events lead to dephosphorylation of myosin light chains, which regulate the contractile state in smooth muscle, and result in vasodilatation.

Pharmacodynamics

Consistent with the symptomatic relief of angina, digital plethysmography indicates that onset of the vasodilatory effect occurs approximately 1 to 3 minutes after sublingual nitroglycerin administration and reaches a maximum by 5 minutes postdose. Effects persist for at least 25 minutes following NITROSTAT administration.

Pharmacokinetics and Drug Metabolism Absorption

Nitroglycerin is rapidly absorbed following sublingual administration of NITROSTAT tablets. Mean peak nitroglycerin plasma concentrations occur at a mean time of approximately 6 to 7 minutes postdose (Table 1). Maximum plasma nitroglycerin concentrations (Cmax) and area under the plasma concentration-time curves (AUC) increase dose-proportionally following 0.3 to 0.6 mg NITROSTAT. The absolute bioavailability of nitroglycerin from NITROSTAT tablets is approximately 40% but tends to be variable due to factors influencing drug absorption, such as sublingual hydration and mucosal metabolism.

Table 1
 | Mean Nitroglycerin (SD) Values
 | 2 × 0.3 mg | 1 × 0.6 mg
Parameter | NITROSTAT Tablets | NITROSTAT Tablets
Cmax, ng/mL | 2.3 (1.7) | 2.1 (1.5)
Tmax, min | 6.4 (2.5) | 7.2 (3.2)
AUC(0–∞), min | 14.9 (8.2) | 14.9 (11.4)
t½, min | 2.8 (1.1) | 2.6 (0.6)

Distribution

The volume of distribution (VArea) of nitroglycerin following intravenous administration is 3.3 L/kg. At plasma concentrations between 50 and 500 ng/mL, the binding of nitroglycerin to plasma proteins is approximately 60%, while that of 1,2- and 1,3-dinitroglycerin is 60% and 30%, respectively.

Metabolism

A liver reductase enzyme is of primary importance in the metabolism of nitroglycerin to glycerol di- and mononitrate metabolites and ultimately to glycerol and organic nitrate. Known sites of extrahepatic metabolism include red blood cells and vascular walls. In addition to nitroglycerin, 2 major metabolites 1,2- and 1,3-dinitroglycerin, are found in plasma. Mean peak 1,2- and 1,3-dinitroglycerin plasma concentrations occur at approximately 15 minutes postdose. The elimination half-life of 1,2- and 1,3-dinitroglycerin is 36 and 32 minutes, respectively. The 1,2- and 1,3-dinitroglycerin metabolites have been reported to possess approximately 2% and 10%, respectively, of the pharmacological activity of nitroglycerin. Higher plasma concentrations of the dinitro metabolites, along with their nearly 10-fold longer elimination half-lives, may contribute significantly to the duration of pharmacologic effect. Glycerol mononitrate metabolites of nitroglycerin are biologically inactive.

Elimination

Nitroglycerin plasma concentrations decrease rapidly, with a mean elimination half-life of 2 to 3 minutes. Half-life values range from 1.5 to 7.5 minutes. Clearance (13.6 L/min) greatly exceeds hepatic blood flow. Metabolism is the primary route of drug elimination.

INDICATIONS AND USAGE

Nitroglycerin is indicated for the acute relief of an attack or acute prophylaxis of angina pectoris due to coronary artery disease.

CONTRAINDICATIONS

Nitroglycerin is contraindicated in patients who are allergic to it.

Sublingual nitroglycerin therapy is contraindicated in patients with early myocardial infarction, severe anemia, increased intracranial pressure, and those with a known hypersensitivity to nitroglycerin.

Administration of NITROSTAT is contraindicated in patients who are using a phosphodiesterase-5 (PDE-5) inhibitor (e.g., sildenafil citrate, tadalafil, vardenafil hydrochloride) since these compounds have been shown to potentiate the hypotensive effects of organic nitrates.

Do not use NITROSTAT in patients who are taking the soluble guanylate cyclase stimulator riociguat. Concomitant use can cause hypotension.

WARNINGS

The benefits of sublingual nitroglycerin in patients with acute myocardial infarction or congestive heart failure have not been established. If one elects to use nitroglycerin in these conditions, careful clinical or hemodynamic monitoring must be used because of the possibility of hypotension and tachycardia.

PRECAUTIONS

General

Only the smallest dose required for effective relief of the acute anginal attack should be used. Excessive use may lead to the development of tolerance. NITROSTAT tablets are intended for sublingual or buccal administration and should not be swallowed.

Severe hypotension, particularly with upright posture, may occur with small doses of nitroglycerin. This drug should therefore be used with caution in patients who may be volume-depleted or who, for whatever reason, are already hypotensive. Hypotension induced by nitroglycerin may be accompanied by paradoxical bradycardia and increased angina pectoris.

Nitrate therapy may aggravate the angina caused by hypertrophic cardiomyopathy.

As tolerance to other forms of nitroglycerin develops, the effects of sublingual nitroglycerin on exercise tolerance, although still observable, is blunted.

In industrial workers who have had long-term exposure to unknown (presumably high) doses of organic nitrates, tolerance rarely occurs. Chest pain, acute myocardial infarction, and even sudden death have occurred during temporary withdrawal of nitrates from these workers, demonstrating the existence of true physical dependence.

Several clinical trials of nitroglycerin patches or infusions in patients with angina pectoris have evaluated regimens that incorporated a 10- to 12-hour nitrate free interval. In some of these trials, an increase in the frequency of anginal attacks during the nitrate free interval was observed in a small number of patients. In one trial, patients had decreased exercise tolerance at the end of the nitrate interval. Hemodynamic rebound has been observed only rarely; on the other hand, few studies were so designed that rebound, if it had occurred, would have been detected.

Nitrate tolerance as a result of sublingual nitroglycerin administration is probably possible, but only in patients who maintain high continuous nitrate levels for more than 10 or 12 hours daily. Such use of sublingual nitroglycerin would entail administration of scores of tablets daily and is not recommended.

The drug should be discontinued if blurring of vision or drying of the mouth occurs. Excessive dosage of nitroglycerin may produce severe headaches.

Information for Patients

NITROSTAT is a sublingual tablet and should not be chewed, crushed, or swallowed.

If possible, patients should sit down when taking NITROSTAT tablets and should use caution when returning to a standing position. This eliminates the possibility of falling due to lightheadedness or dizziness.

One tablet should be dissolved under the tongue or in the buccal pouch at the first sign of an acute anginal attack. The dose may be repeated approximately every 5 minutes until relief is obtained.

If chest pain persists after a total of 3 tablets in a 15-minute period, or if the pain is different than is typically experienced, prompt medical attention is recommended.

NITROSTAT may be used prophylactically 5 to 10 minutes prior to engaging in activities that might precipitate an acute attack.

Nitroglycerin may produce a burning or tingling sensation when administered sublingually; however, the ability to produce a burning or tingling sensation should not be considered a reliable method for determining the potency of the tablets.

Headaches can sometimes accompany treatment with nitroglycerin. In patients who get these headaches, the headaches may be a marker of the activity of the drug.

Treatment with nitroglycerin may be associated with lightheadedness upon standing, especially just after rising from a recumbent or seated position. This effect may be more frequent in patients who have also consumed alcohol.

Nitroglycerin should be kept in the original glass container and must be tightly capped after each use to prevent loss of tablet potency.

Drug Interactions

Concomitant use of NITROSTAT with soluble guanylate cyclase stimulators is contraindicated (see CONTRAINDICATIONS).

Concomitant use of nitrates and alcohol may cause hypotension.

The vasodilatory and hemodynamic effects of nitroglycerin may be enhanced by concomitant administration of aspirin.

Intravenous administration of nitroglycerin decreases the thrombolytic effect of alteplase. Therefore, caution should be observed in patients receiving sublingual nitroglycerin during alteplase therapy.

Intravenous nitroglycerin reduces the anticoagulant effect of heparin and activated partial thromboplastin times (APTT) should be monitored in patients receiving heparin and intravenous nitroglycerin. It is not known if this effect occurs following single sublingual nitroglycerin doses.

Tricyclic antidepressants (amitriptyline, desipramine, doxepin, others) and anticholinergic drugs may cause dry mouth and diminished salivary secretions. This may make dissolution of sublingual nitroglycerin difficult. Increasing salivation with chewing gum or artificial saliva products may prove useful in aiding dissolution of sublingual nitroglycerin.

Oral administration of nitroglycerin markedly decreases the first-pass metabolism of dihydroergotamine and subsequently increases its oral bioavailability. Ergotamine is known to precipitate angina pectoris. Therefore, patients receiving sublingual nitroglycerin should avoid ergotamine and related drugs or be monitored for symptoms of ergotism if this is not possible.

Administration of nitroglycerin is contraindicated in patients who are using PDE-5 inhibitors (e.g., sildenafil citrate, tadalafil, vardenafil hydrochloride). These compounds have been shown to potentiate the hypotensive effects of organic nitrates.

A decrease in therapeutic effect of sublingual nitroglycerin may result from use of long-acting nitrates.

Drug/Laboratory Test Interactions

Nitrates may interfere with the Zlatkis-Zak color reaction, causing a false report of decreased serum cholesterol.

Carcinogenesis, Mutagenesis, Impairment of Fertility

Animal carcinogenesis studies with sublingually administered nitroglycerin have not been performed.

Carcinogenicity potential of nitroglycerin was evaluated in rats receiving up to 434 mg/kg/day of dietary nitroglycerin for 2 years. Rats developed dose-related fibrotic and neoplastic changes in liver, including carcinomas, and interstitial cell tumors in testes. At high dose, the incidences of hepatocellular carcinomas in males was 48% and in females was 33%, compared to 0% in untreated controls. Incidences of testicular tumors were 52% vs. 8% in controls. Lifetime dietary administration of up to 1058 mg/kg/day of nitroglycerin was not tumorigenic in mice.

Nitroglycerin was mutagenic in Ames tests performed in 2 different laboratories. Nevertheless, there was no evidence of mutagenicity in an in vivo dominant lethal assay with male rats treated with doses up to about 363 mg/kg/day, PO, or in ex vivo cytogenetic tests in rat and dog cells.

In a 3-generation reproduction study, rats received dietary nitroglycerin at doses up to about 434 mg/kg/day for 6 months prior to mating of the F0 generation, with treatment continuing through successive F1 and F2 generations. The high dose was associated with decreased feed intake and body weight gain in both sexes at all matings. No specific effect on the fertility of the F0 generation was seen. Infertility noted in subsequent generations, however, was attributed to increased interstitial cell tissue and aspermatogenesis in the high-dose males. In this 3-generation study, there was no clear evidence of teratogenicity.

Pregnancy Category B

Animal reproduction and teratogenicity studies have not been conducted with nitroglycerin sublingual tablets. However, teratology studies conducted in rats and rabbits with topically applied nitroglycerin ointment at dosages up to 80 mg/kg/day and 240 mg/kg/day, respectively revealed no toxic effects on dams or fetuses.

There are no adequate and well-controlled studies in pregnant women. Nitroglycerin should be given to a pregnant woman only if clearly needed.

Nursing Mothers

It is not known whether nitroglycerin is excreted in human milk. Because many drugs are excreted in human milk, caution should be exercised when nitroglycerin is administered to a nursing woman.

Pediatric Use

The safety and effectiveness of nitroglycerin in pediatric patients have not been established.

Geriatric Use

Clinical studies of NITROSTAT did not include sufficient numbers of subjects aged 65 and over to determine whether they respond differently from younger subjects. Other reported clinical experience has not identified differences in responses between the elderly and younger patients. In general, dose selection for an elderly patient should be cautious, usually starting at the low end of the dosing range, reflecting the greater frequency of decreased hepatic, renal, or cardiac function, and of concomitant disease or other drug therapy.

ADVERSE REACTIONS

Headache that may be severe and persistent may occur immediately after use. Vertigo, dizziness, weakness, palpitation, and other manifestations of postural hypotension may develop occasionally, particularly in erect, immobile patients. Marked sensitivity to the hypotensive effects of nitrates (manifested by nausea, vomiting, weakness, diaphoresis, pallor, and collapse) may occur at therapeutic doses. Syncope due to nitrate vasodilatation has been reported. Flushing, drug rash, and exfoliative dermatitis have been reported in patients receiving nitrate therapy.

OVERDOSAGE

Hemodynamic Effects: The effects of nitroglycerin overdose are generally the results of nitroglycerin's capacity to induce vasodilatation, venous pooling, reduced cardiac output, and hypotension. These hemodynamic changes may have protean manifestations, including increased intracranial pressure, with any or all of persistent throbbing headache, confusion, and moderate fever; vertigo; palpitations; tachycardia; visual disturbances; nausea and vomiting (possibly with colic and even bloody diarrhea); syncope (especially in the upright posture); dyspnea, later followed by reduced ventilatory effort; diaphoresis, with the skin either flushed or cold and clammy; heart block and bradycardia; paralysis; coma; seizures; and death.

No specific antagonist to the vasodilator effects of nitroglycerin is known, and no intervention has been subject to controlled study as a therapy of nitroglycerin overdose. Because the hypotension associated with nitroglycerin overdose is the result of venodilatation and arterial hypovolemia, prudent therapy in this situation should be directed toward increase in central fluid volume. Passive elevation of the patient's legs may be sufficient, but intravenous infusion of normal saline or similar fluid may also be necessary.

The use of epinephrine or other arterial vasoconstrictors in this setting is likely to do more harm than good.

In patients with renal disease or congestive heart failure, therapy resulting in central volume expansion is not without hazard. Treatment of nitroglycerin overdose in these patients may be subtle and difficult, and invasive monitoring may be required.

Methemoglobinemia: Methemoglobinemia has been rarely reported in association with organic nitrates. The diagnosis should be suspected in patients who exhibit signs of impaired oxygen delivery despite adequate cardiac output and adequate arterial PO2. Classically, methemoglobinemic blood is described as chocolate brown, without color change on exposure to air.

If methemoglobinemia is present, intravenous administration of methylene blue, 1 to 2 mg/kg of body weight, may be required.

DOSAGE AND ADMINISTRATION

One tablet should be dissolved under the tongue or in the buccal pouch at the first sign of an acute anginal attack. The dose may be repeated approximately every 5 minutes until relief is obtained. If the pain persists after a total of 3 tablets in a 15-minute period, or if the pain is different than is typically experienced, prompt medical attention is recommended. NITROSTAT may be used prophylactically 5 to 10 minutes prior to engaging in activities that might precipitate an acute attack.

During administration the patient should rest, preferably in the sitting position.

No dosage adjustment is required in patients with renal failure.

HOW SUPPLIED

NITROSTAT is supplied as white, round, flat-faced tablets in 3 strengths (0.3 mg, 0.4 mg, and 0.6 mg) in bottles containing 100 tablets each, with color-coded labels, and in color-coded Patient Convenience Packages of 4 bottles of 25 tablets each.

0.4 mg: | Coded "N" on one side and "4" on the other. NDC 63187-884-25—Bottle of 25

STORAGE AND HANDLING

Store at Controlled Room Temperature 20°–25°C (68°–77°F) [see USP].

Rx only

LAB-0180-7.0

January 2017

Relabeled by Proficient Rx LP, Thousand Oaks, CA 91320

Nitrostat® (Nitroglycerin Sublingual Tablets, USP)

Read this information carefully before you start NITROSTAT® (NYE-troe-stat) and each time you refill your prescription. There may be new information. This information does not replace talking with your doctor. If you have any questions about NITROSTAT, ask your doctor. Your doctor will know if NITROSTAT is right for you.

What is NITROSTAT?

NITROSTAT is a type of medicine known as an organic nitrate and is a vasodilating agent. It is used to treat a type of chest pain called angina.

What is Angina?

Angina is a pain or discomfort that keeps coming back when part of your heart does not get enough blood. Angina feels like a pressing or squeezing pain, usually in your chest under the breastbone. Sometimes you can feel it in your shoulders, arms, neck, jaws, or back. NITROSTAT can relieve this pain.

Who should not use NITROSTAT?

Do not use NITROSTAT if you are allergic to organic nitrates (like the active ingredient in NITROSTAT).

You should not take NITROSTAT if you have the following conditions:

- very recent heart attack
- severe anemia
- increased pressure in the head

Do not take NITROSTAT with drugs for erectile dysfunction, like VIAGRA® (sildenafil citrate), CIALIS® (tadalafil), or LEVITRA® (vardenafil hydrochloride), as this may lead to extreme lowering of your blood pressure.

Do not take NITROSTAT if you take medicines called guanylate cyclase stimulators which include riociguat, a medicine that treats pulmonary arterial hypertension and chronic-thromboembolic pulmonary hypertension.

What should I tell my doctor before taking NITROSTAT?

Before using NITROSTAT, tell your doctor if:

- You are taking any medicines that are used to treat angina, heart failure, or an irregular heartbeat.
- You are taking any medicines that reduce blood pressure.
- You are taking any diuretics (water pills).
- You are taking medications to treat depression or psychiatric illness.
- You are taking ergotamine or similar drugs for migraine headaches.
- You are taking aspirin.
- You are taking the blood thinner medicine heparin.
- You are taking any medicines for erectile dysfunction.
- You are pregnant or plan to become pregnant.
- You are breastfeeding.

How should I take NITROSTAT?

- Do not chew, crush, or swallow NITROSTAT tablets.
- You should sit down when taking NITROSTAT tablets and use caution when you stand up. This eliminates the possibility of falling due to lightheadedness or dizziness.
- One tablet should be dissolved under the tongue or in the oral cavity at the first sign of chest pain.
- The dose may be repeated approximately every 5 minutes, until the chest pain is relieved.
- If the pain persists after a total of 3 tablets in a 15-minute period, or is different than you typically experience, call your doctor or seek emergency help.
- NITROSTAT may be used 5 to 10 minutes prior to activities that might cause chest pain.
- You may feel a burning or tingling sensation in your mouth when you take NITROSTAT.

What should I avoid while taking NITROSTAT?

- Do not breastfeed. It is not known if NITROSTAT will pass through your milk.
- Do not consume alcohol while taking NITROSTAT, as this can lower your blood pressure.
- Do not start any new prescription or non-prescription medicines or supplements, unless you check with your doctor first.

What are the possible side effects of NITROSTAT?

NITROSTAT may cause the following side effects:

- headache
- vertigo (a major symptom of balance disorder)
- dizziness
- weakness
- heart palpitations (unusual awareness of the heartbeat)
- low blood pressure upon rising from a seated position
- nausea and vomiting
- sweating
- paleness
- fainting
- flushing (warm or red condition of your skin)
- other skin reactions that may be severe

NITROSTAT may cause a false test result of decreased serum cholesterol.

Tell your doctor if you are concerned about any side effects you experience. These are not all the possible side effects of NITROSTAT. For a complete list, ask your doctor or pharmacist.

How do I store NITROSTAT?

NITROSTAT should be kept in the original glass container and tightly capped after each use to prevent loss of tablet potency.

Store NITROSTAT tablets at room temperature (between 68° and 77°F).

General advice about NITROSTAT

Sometimes doctors will prescribe a medicine for a condition that is not included in the patient information leaflets. Only use NITROSTAT the way your doctor told you to. Do not give NITROSTAT to other people, even if they have the same symptoms you have. It may harm them.

You can ask your pharmacist or doctor for information about NITROSTAT, or you can visit the Pfizer website at www.pfizer.com or call 1-800-438-1985.

LAB-0422-2.0
January 2017

Relabeled By:

Proficient Rx LP

Thousand Oaks, CA 91320

PRINCIPAL DISPLAY PANEL - 0.4 mg Tablet Bottle Label

ALWAYS DISPENSE WITH
PATIENT PACKAGE INSERT

NDC 63187-884-25

Nitrostat®
(Nitroglycerin Sublingual
Tablets, USP)

0.4 mg / tablet

25 Sublingual Tablets
Rx only